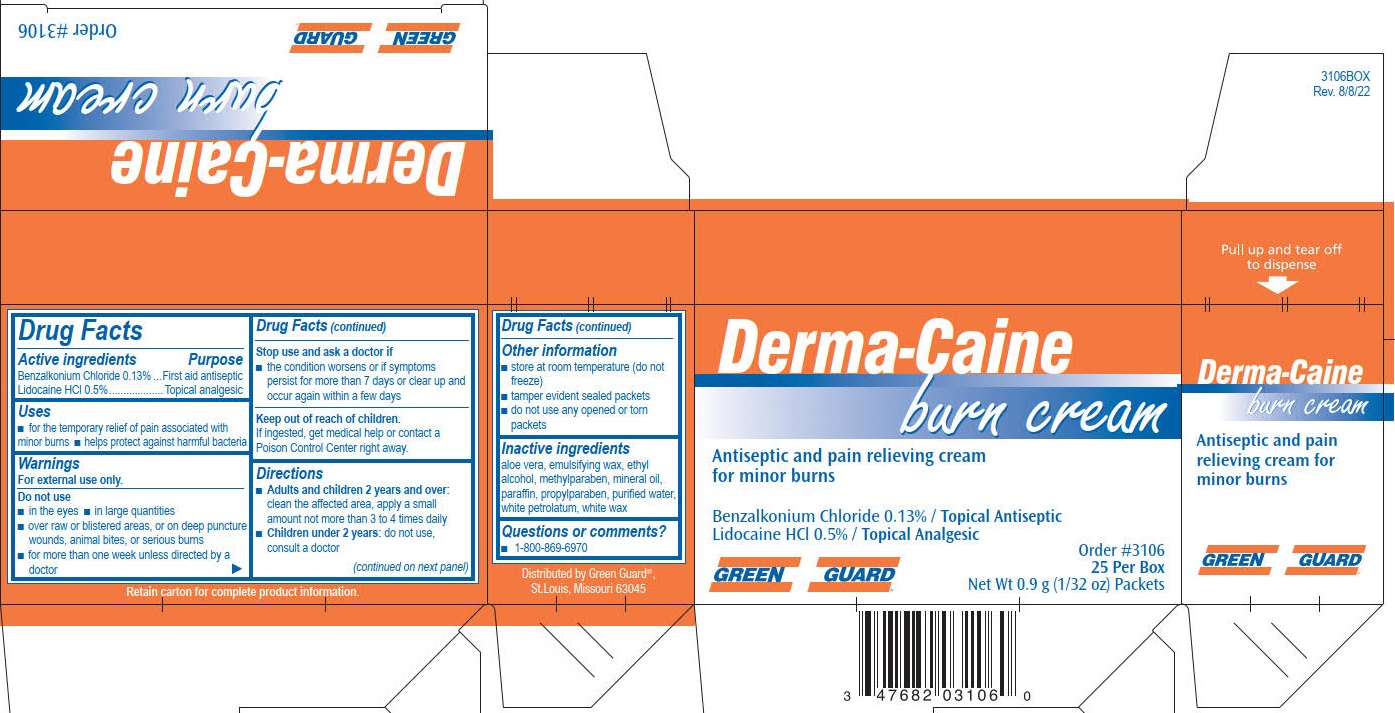 DRUG LABEL: Green Guard Derma-Caine Burn
NDC: 47682-319 | Form: CREAM
Manufacturer: Unifirst First Aid Corporation
Category: otc | Type: HUMAN OTC DRUG LABEL
Date: 20250908

ACTIVE INGREDIENTS: BENZALKONIUM CHLORIDE 1.3 mg/1 g; LIDOCAINE HYDROCHLORIDE 5 mg/1 g
INACTIVE INGREDIENTS: MINERAL OIL; PROPYLPARABEN; ALOE VERA LEAF; METHYLPARABEN; PARAFFIN; WHITE WAX; ALCOHOL; PETROLATUM; WATER

Green Guard Derma-Caine

Active ingredients

Benzalkonium chloride 0.13%

Lidocaine HCl 0.5%

Purpose

Topical analgesic

Uses

First aid to help prevent infection in minor cuts, scrapes and burns.

For the temporary relief of pain or itching associated with:

- sunburn
- minor burns
- insect bites
- minor skin irritation
- cuts
- scrapes

Warnings

For external use only.

Do not use

- in the eyes
- over large areas of the body or on deep puncture wounds, animal bites or serious burns
- in large quantities, particularly over raw surfaces or blistered areas

Stop use and ask a doctor if

- the condition gets worse
- condition clears up and recurs within a few days
- condition persists for more than 7 days

PREGNANCY OR BREAST FEEDING

If pregnant or breast feeding, ask a health care professional before use.

Keep out of reach of children.

If swallowed, get medical help or contact a Poison Control Center right away.

Directions

Adults and children 12 years and over:

- clean the affected area
- apply a small amount of this product on the area 3 to 4 times daily
- may be covered with a sterile bandage

Children under 12 years:

- consult a doctor

Other information

- store in a cool, dry area 59° to 79° F (15° to 25°C)
- tamper evident sealed packets
- do not use any opened or torn packets

Inactive ingredients

decolorized aloe vera, emulsifying wax, ethyl alcohol, methylparaben, mineral oil, paraffin, petrolatum, propylparaben, purified water, white petrolatum, white wax

Questions or comments? 1-800-869-6970

Green Guard Derma-Caine Burn Cream Label

Green Guard

Derma-Caine burn cream

Antiseptic and pain relieving cream for monor cuts, scrapes and burns

Benzalkonium Chloride 0.13%/Topical Antiseptic

Lidocaine HCl 0.5%/Topical Analgesic

0.9 Gram 25 Single Dose Packets

Reorder #3106

Distributed by Green Guard®, Str. Louis, Missouri 63045